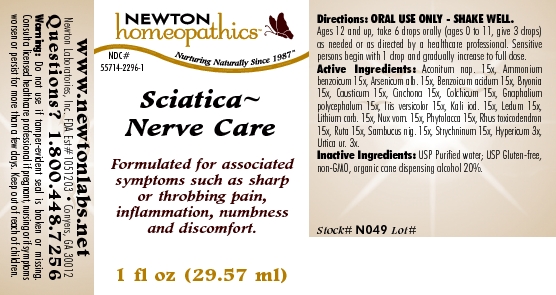 DRUG LABEL: Sciatica - Nerve Care 
NDC: 55714-2296 | Form: LIQUID
Manufacturer: Newton Laboratories, Inc.
Category: homeopathic | Type: HUMAN OTC DRUG LABEL
Date: 20110301

ACTIVE INGREDIENTS: Aconitum Napellus 15 [hp_X]/1 mL; Ammonium Benzoate 15 [hp_X]/1 mL; Arsenic Trioxide 15 [hp_X]/1 mL; Benzoic Acid 15 [hp_X]/1 mL; Bryonia Alba Root 15 [hp_X]/1 mL; Causticum 15 [hp_X]/1 mL; Cinchona Officinalis Bark 15 [hp_X]/1 mL; Colchicum Autumnale Bulb 15 [hp_X]/1 mL; Pseudognaphalium Obtusifolium 15 [hp_X]/1 mL; Iris Versicolor Root 15 [hp_X]/1 mL; Potassium Iodide 15 [hp_X]/1 mL; Ledum Palustre Twig 15 [hp_X]/1 mL; Lithium Carbonate 15 [hp_X]/1 mL; Strychnos Nux-vomica Seed 15 [hp_X]/1 mL; Phytolacca Americana Root 15 [hp_X]/1 mL; Toxicodendron Pubescens Leaf 15 [hp_X]/1 mL; Ruta Graveolens Flowering Top 15 [hp_X]/1 mL; Sambucus Nigra Flowering Top 15 [hp_X]/1 mL; Strychnine 15 [hp_X]/1 mL; Hypericum Perforatum 3 [hp_X]/1 mL; Urtica Urens 3 [hp_X]/1 mL
INACTIVE INGREDIENTS: Alcohol

Sciatica - Nerve Care

INDICATIONS & USAGE SECTION

Sciatica - Nerve Care Formulated for associated symptoms such as sharp or throbbing pain, inflammation, numbness and discomfort.

DOSAGE & ADMINISTRATION SECTION

Directions: ORAL USE ONLY - SHAKE WELL. Ages 12 and up, take 6 drops orally (ages 0 to 11, give 3 drops) as needed or as directed by a healthcare professional. Sensitive persons begin with 1 drop and gradually increase to full dose.

OTC - ACTIVE INGREDIENT SECTION

Aconitum nap. 15x, Ammonium benzoicum 15x, Arsenicum alb. 15x, Benzoicum acidum 15x, Bryonia15x, Causticum 15x, Cinchona 15x, Colchicum 15x, Gnaphalium polycephalum 15x, Iris versicolor 15x, Kali iod. 15x, Ledum 15x, Lithium carb. 15x, Nux vom. 15x, Phytolacca 15x, Rhus toxicodendron 15x, Ruta 15x, Sambucus nig. 15x, Strychninum 15x, Hypericum 3x, Urtica ur. 3x.

OTC - PURPOSE SECTION

Formulated for associated symptoms such as sharp or throbbing pain, inflammation, numbness and discomfort.

INACTIVE INGREDIENT SECTION

Inactive Ingredients: USP Purified Water; USP Gluten-free, non-GMO, organic cane dispensing alcohol 20%.

QUESTIONS SECTION

www.newtonlabs.net Newton Laboratories, Inc. FDA Est # 1051203 - Conyers, GA 30012
Questions? 1.800.448.7256

WARNINGS SECTION

Warning: Do not use if tamper - evident seal is broken or missing. Consult a licensed healthcare professional if pregnant, nursing or if symptoms worsen or persist for more than a few days. Keep out of reach of children.

OTC - PREGNANCY OR BREAST FEEDING SECTION

Consult a licensed healthcare professional if pregnant, nursing or if symptoms worsen or persist for more than a few days.

OTC - KEEP OUT OF REACH OF CHILDREN SECTION

Keep out of reach of children.